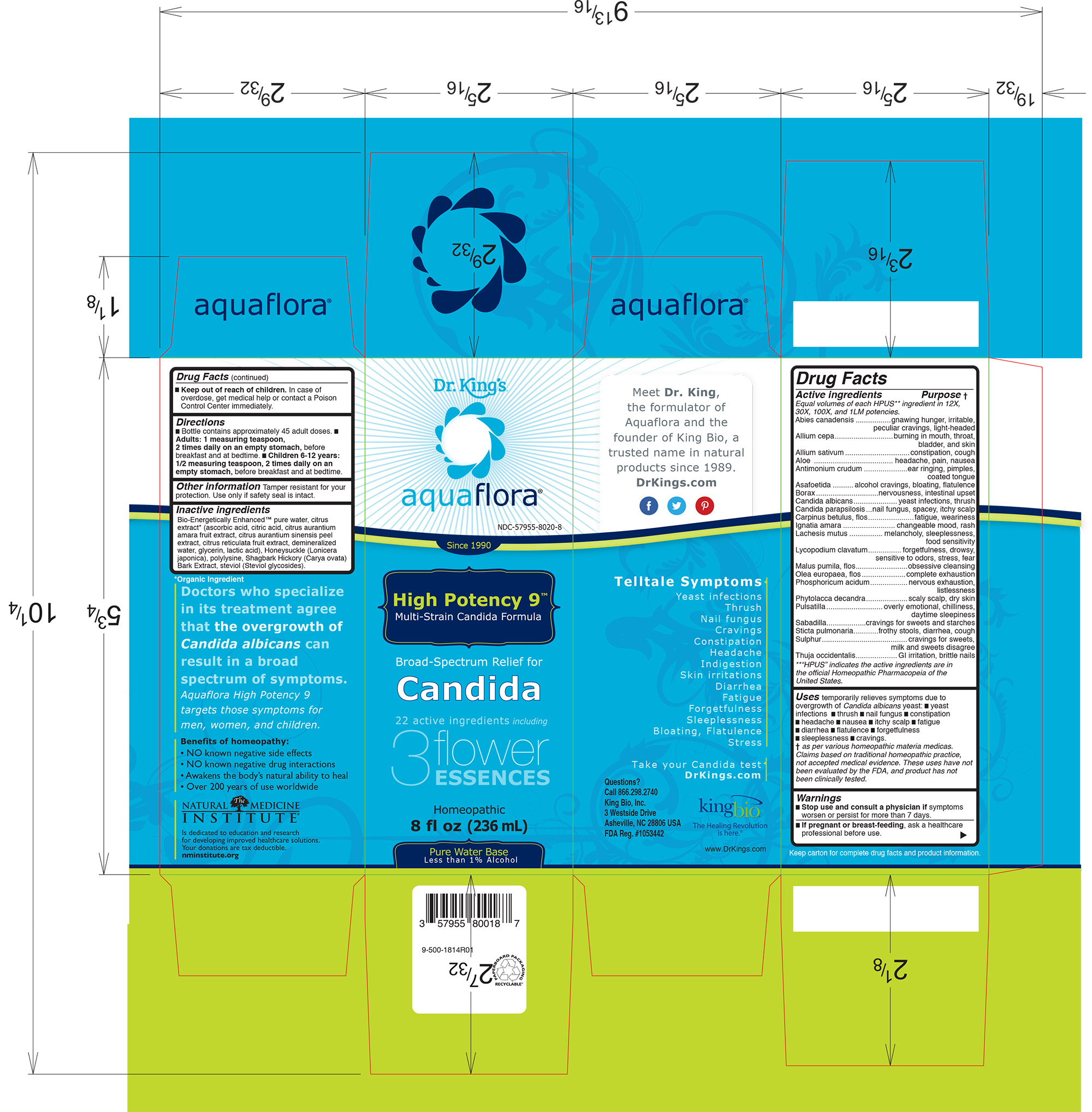 DRUG LABEL: Candida High Potency 9
NDC: 57955-8020 | Form: LIQUID
Manufacturer: King Bio Inc.
Category: homeopathic | Type: HUMAN OTC DRUG LABEL
Date: 20210222

ACTIVE INGREDIENTS: LOBARIA PULMONARIA 12 [hp_X]/236 mL; SULFUR 12 [hp_X]/236 mL; THUJA OCCIDENTALIS LEAF 12 [hp_X]/236 mL; TSUGA CANADENSIS FLOWER BUD 12 [hp_X]/236 mL; ONION 12 [hp_X]/236 mL; GARLIC 12 [hp_X]/236 mL; ALOE 12 [hp_X]/236 mL; ANTIMONY TRISULFIDE 12 [hp_X]/236 mL; FERULA ASSA-FOETIDA RESIN 12 [hp_X]/236 mL; SODIUM BORATE 12 [hp_X]/236 mL; CANDIDA ALBICANS 12 [hp_X]/236 mL; CANDIDA PARAPSILOSIS 12 [hp_X]/236 mL; CARPINUS BETULUS FLOWERING TOP 12 [hp_X]/236 mL; STRYCHNOS IGNATII SEED 12 [hp_X]/236 mL; LACHESIS MUTA VENOM 12 [hp_X]/236 mL; LYCOPODIUM CLAVATUM SPORE 12 [hp_X]/236 mL; MALUS PUMILA FLOWER 12 [hp_X]/236 mL; OLEA EUROPAEA FLOWER 12 [hp_X]/236 mL; PHOSPHORIC ACID 12 [hp_X]/236 mL; PHYTOLACCA AMERICANA ROOT 12 [hp_X]/236 mL; ANEMONE PULSATILLA 12 [hp_X]/236 mL; SCHOENOCAULON OFFICINALE SEED 12 [hp_X]/236 mL
INACTIVE INGREDIENTS: WATER; CARYA OVATA BARK; CITRUS BIOFLAVONOIDS; LONICERA JAPONICA FLOWER; REBAUDIOSIDE A

Candida High Potency 9

Active Ingredients

HPUS active ingredients in equal potencies of 12X, 30X, 100X and 1LM

Abies canadensis

Allium cepa

Allium sativum

Aloe

Antimonium crudum

Asafoetida

Borax

Candida albicans

Candida parapsilosis

Carpinus betulus, flos

Ignatia amara

Lachesis mutus

Lycopodium clavatum

Malus pumila, flos

Olea europaea, flos

Phosphoricum acidum

Phytolacca decandra

Pulsatilla

Sabadilla

Sticta pulmonaria

Sulphur

Thuja occidentalis

Inactive Ingredients

Inactive Ingredient

Bio-Energetically Enhanced™ pure water, citrus
extract* (ascorbic acid, citric acid, citrus aurantium
amara fruit extract, citrus aurantium sinensis peel
extract, citrus reticulata fruit extract, demineralized
water, glycerin, lactic acid), Honeysuckle (Lonicera
japonica), polylysine, Shagbark Hickory (Carya ovata)
Bark Extract, steviol (Steviol glycosides).

Directions

- Bottle contains approximately 45 adult doses.
- Adults: 1 measuring teaspoon, 2 times daily on an empty stomach, before breakfast and at bedtime.
- Children 6-12 years: 1/2 measuring teaspoon, 2 times daily on an empty stomach, before breakfast and at bedtime.

Purpose

Equal volumes of each HPUS** ingredient in 12X,
30X, 100X, and 1LM potencies.
Abies canadensis .................gnawing hunger, irritable,
peculiar cravings, light-headed
Allium cepa............................burning in mouth, throat,
bladder, and skin
Allium sativum...............................constipation, cough
Aloe ...................................... headache, pain, nausea
Antimonium crudum .....................ear ringing, pimples,
coated tongue
Asafoetida ..........alcohol cravings, bloating, flatulence
Borax..............................nervousness, intestinal upset
Candida albicans.....................yeast infections, thrush
Candida parapsilosis...nail fungus, spacey, itchy scalp
Carpinus betulus, flos......................fatigue, weariness
Ignatia amara ......................... changeable mood, rash
Lachesis mutus ................ melancholy, sleeplessness,
food sensitivity
Lycopodium clavatum................forgetfulness, drowsy,
sensitive to odors, stress, fear
Malus pumila, flos.........................obsessive cleansing
Olea europaea, flos.....................complete exhaustion
Phosphoricum acidum.................. nervous exhaustion,
listlessness
Phytolacca decandra....................scaly scalp, dry skin
Pulsatilla...........................overly emotional, chilliness,
daytime sleepiness
Sabadilla...................cravings for sweets and starches
Sticta pulmonaria............frothy stools, diarrhea, cough
Sulphur.........................................cravings for sweets,
milk and sweets disagree
Thuja occidentalis....................GI irritation, brittle nails
**“HPUS” indicates the active ingredients are in
the official Homeopathic Pharmacopeia of the
United States.

Warnings

Stop use and consult a physician if symptoms
worsen or persist for more than 7 days.

If pregnant or breast-feeding, ask a healthcare
professional before use.

Keep out of reach of children. In case of
overdose, get medical help or contact a Poison
Control Center immediately.

Other Information

Tamper resistant for your protection. Use only if safety seal is intact.

Uses

temporarily relieves symptoms due to
overgrowth of Candida albicans yeast: █ yeast
infections █ thrush █ nail fungus █ constipation
█ headache █ nausea █ itchy scalp █ fatigue
█ diarrhea █ flatulence █ forgetfulness
█ sleeplessness █ cravings.
† as per various homeopathic materia medicas.
Claims based on traditional homeopathic practice,
not accepted medical evidence. These uses have not
been evaluated by the FDA, and product has not
been clinically tested.